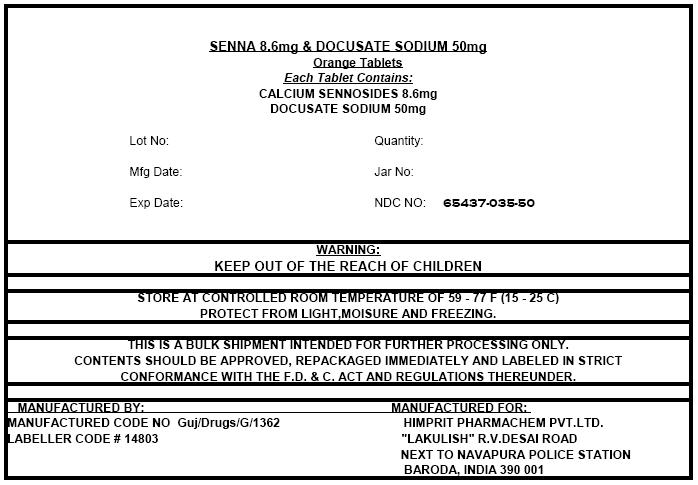 DRUG LABEL: SENNA LEAF and DOCUSATE SODIUM
NDC: 65437-035 | Form: TABLET, FILM COATED
Manufacturer: HIMPRIT PHARMACHEM PVT LTD
Category: otc | Type: HUMAN OTC DRUG LABEL
Date: 20100305

ACTIVE INGREDIENTS: SENNA LEAF 8.6 mg/1 1; DOCUSATE SODIUM 50 mg/1 1
INACTIVE INGREDIENTS: MALTODEXTRIN; CELLULOSE, MICROCRYSTALLINE; ANHYDROUS DIBASIC CALCIUM PHOSPHATE; CROSCARMELLOSE SODIUM; STEARIC ACID; POLYETHYLENE GLYCOL; D&C YELLOW NO. 10; TITANIUM DIOXIDE; WATER; SILICON DIOXIDE; MAGNESIUM STEARATE; HYPROMELLOSE; CARNAUBA WAX

SENNA 8.6mg & DOCUSATE SODIUM 50mg

Drug Facts

ACTIVE INGREDIENT

Active ingredients (in each tablet) | Purpose
Docusate sodium 50 mg | Stool softener
Sennosides 8.6 mg | Laxative

Uses

- relieves occasional constipation (irregularity)
- generally produces a bowel movement in 6-12 hours

Warnings

Do not use

- if you are now taking mineral oil, unless directed by a doctor
- laxative products for longer than 1 week unless directed by a doctor

Ask a doctor before use if you have

- stomach pain
- nausea
- vomiting
- noticed a sudden change in bowel habits that continues over a period of 2 weeks

Stop use and ask a doctor if you have rectal bleeding or fail to have a bowel movement after use of a laxative. These may indicate a serious condition.

PREGNANCY OR BREAST FEEDING

If pregnant or breast-feeding, ask a health professional before use.

Keep out of reach of children. In case of overdose, get medical help or contact a Poison Control Center right away.

Directions

- take preferably at bedtime or as directed by a doctor

age | starting dosage | maximum dosage
adults and children 12 years of age or older | 2 tablets once a day | 4 tablets twice a day
children 6 to under 12 years | 1 tablet once a day | 2 tablets twice a day
children 2 to under 6 years | 1/2 tablet once a day | 1 tablet twice a day
children under 2 years | ask a doctor | ask a doctor

Inactive Ingredients

carnauba wax, colloidal silicon dioxide, croscarmellose sodium, dicalcium phosphate, D&C Yellow #10 Aluminum Lake, FD&C Yellow #6 Aluminum Lake, hypromellose, lactose anhydrous, magnesium stearate, microcrystalline cellulose, PEG 8000, sodium benzoate, stearic acid, tartaric acid, titanium dioxide

PRINCIPAL DISPLAY PANEL - Shipping Label

SENNA 8.6mg & DOCUSATE SODIUM 50mg
Orange Tablets
Each Tablet Contains:
CALCIUM SENNOSIDES 8.6mg
DOCUSATE SODIUM 50mg

Lot No: | Quantity:
Mfg Date: | Jar No:
Exp Date: | NDC NO: 65437-035-50

WARNING:
KEEP OUT OF THE REACH OF CHILDREN

STORE AT CONTROLLED ROOM TEMPERATURE OF 59 - 77 F (15 - 25 C)
PROTECT FROM LIGHT,MOISURE AND FREEZING.

THIS IS A BULK SHIPMENT INTENDED FOR FURTHER PROCESSING ONLY.
CONTENTS SHOULD BE APPROVED, REPACKAGED IMMEDIATELY AND LABELED IN STRICT
CONFORMANCE WITH THE F.D. & C. ACT AND REGULATIONS THEREUNDER.

MANUFACTURED BY:
MANUFACTURED CODE NO Guj/Drugs/G/1362
LABELLER CODE # 14803

MANUFACTURED FOR:
HIMPRIT PHARMACHEM PVT.LTD.
"LAKULISH" R.V.DESAI ROAD
NEXT TO NAVAPURA POLICE STATION
BARODA, INDIA 390 001